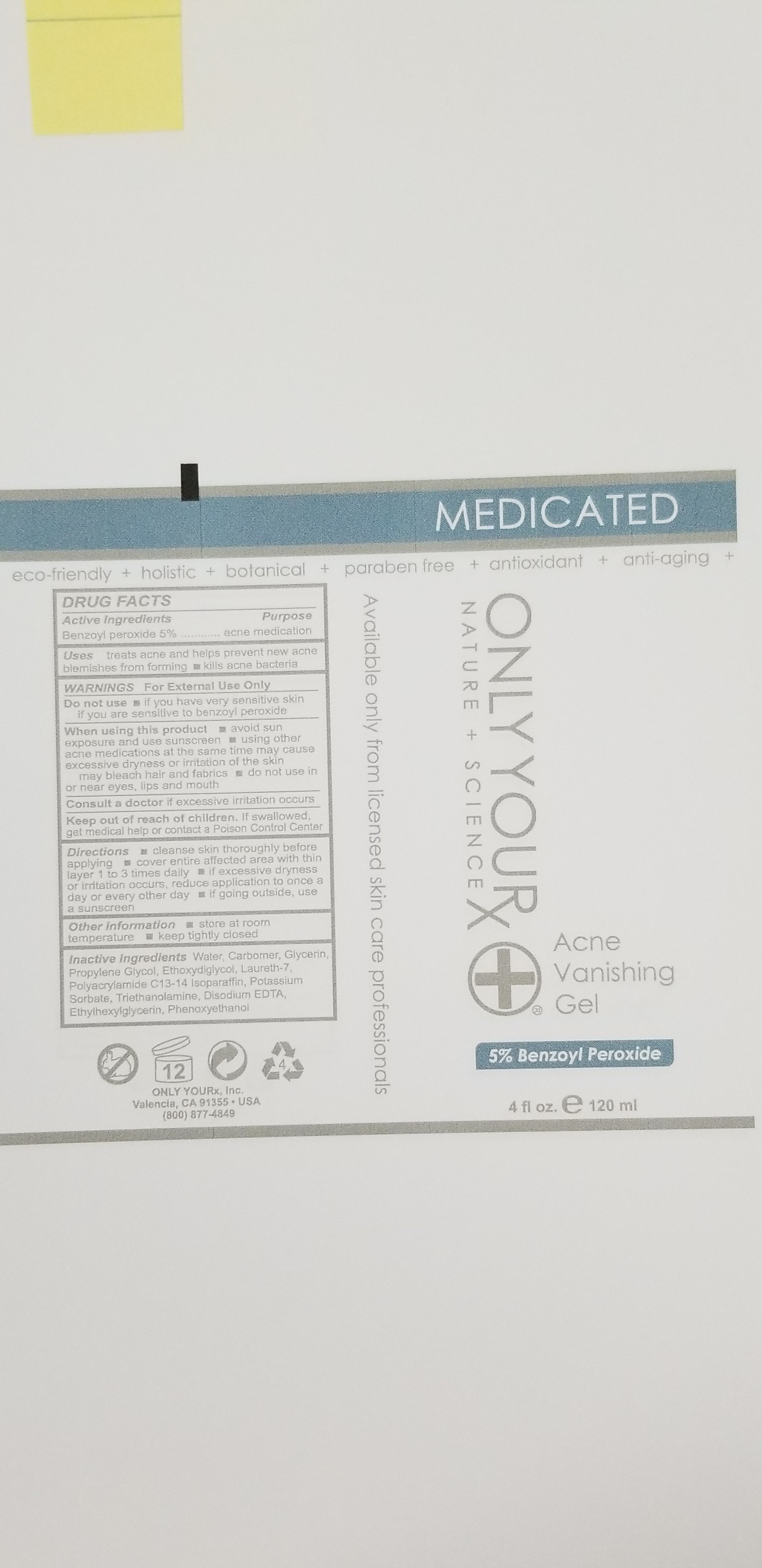 DRUG LABEL: Acne Vanishing Gel- 5%
NDC: 70367-002 | Form: GEL
Manufacturer: Only Yourx, Inc.
Category: otc | Type: HUMAN OTC DRUG LABEL
Date: 20200123

ACTIVE INGREDIENTS: BENZOYL PEROXIDE 5 g/100 mL
INACTIVE INGREDIENTS: AMINOMETHYLPROPANOL; PROPYLENE GLYCOL 1-(2-METHYLBUTYRATE); POTASSIUM SORBATE; LAURETH-7; C13-14 ISOPARAFFIN; GLYCERIN; PHENOXYETHANOL; ETHYLHEXYLGLYCERIN; MAGNESIUM DISODIUM EDTA

ACTIVE INGREDIENT

Benzoyl Peroxide 5%

INACTIVE INGREDIENT

Water, Carbomer, Glycerin, Propylene Glycol, Ethoxydigiycol, Laureth-7, Polyacrylamide C13-14 Isoparaffin, Potassium Sorbate, Triethanolamine, Disodium EDTA, Ethylhexylglycerin, Phenoxyethanol

PURPOSE

Acne Medication

INDICATIONS AND USAGE

treats acne and helps prevent new acne blemishes from forming

kills acne bacteria

Directions:

- Cleanse skin thoroughy before applying
- Cover entire affected area with thin layer 1 to 3 times daily
- If excessive dryness or irritation occurs, reduce application to once a day or every other day
- If going outside, use a sunscreen

Keep out of reach of children. If swallowed, get medical help or contact a Poison Control Center

WARNINGS: For External Use Only

Other Information

- Store at room temperature
- Keep tightly closed

Do not use

- If you have very sensitive skin
- If you are sensitive to benzoyl peroxide

When using this product:

- avoid sun exposure and use sunscreen
- using other acne medications at the same time may cause excessive dryness or irritation of the skin
- may bleach hair and fabrics
- do not use in or near eyes, lips and mouth

Consult a doctor if excessive irritation occurs